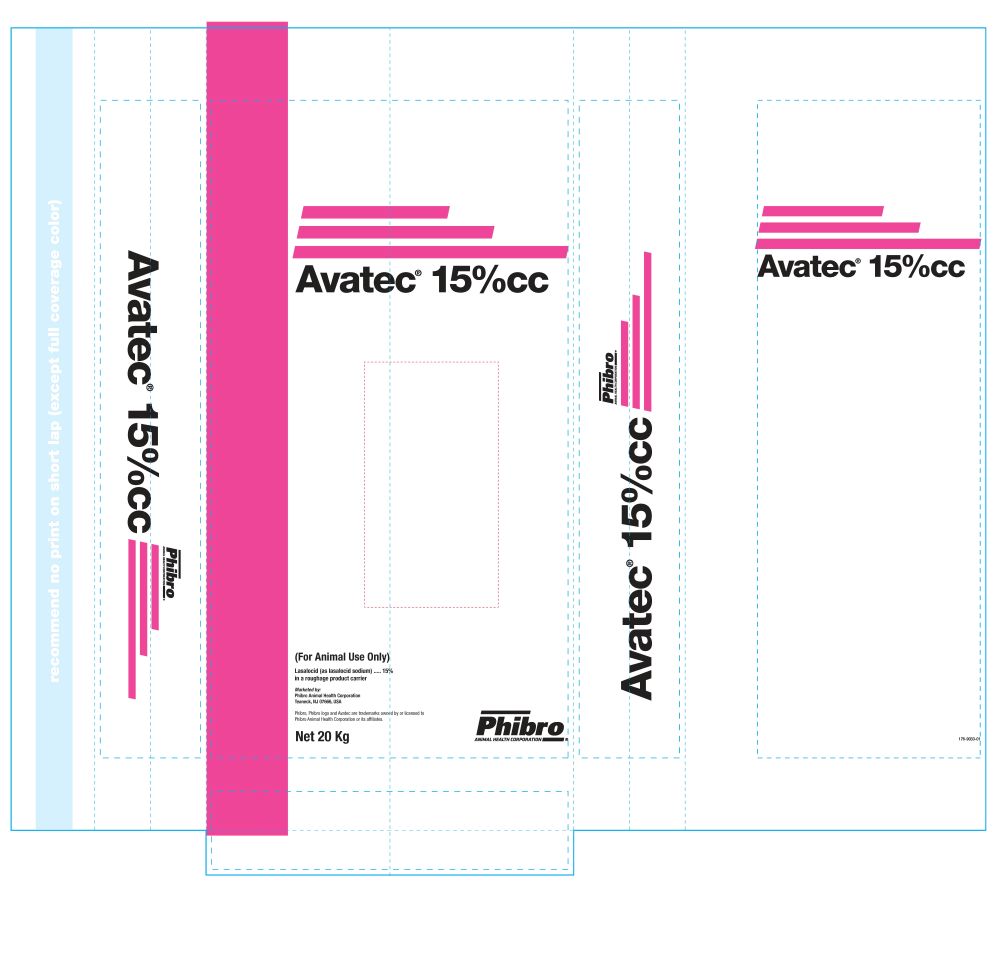 DRUG LABEL: Avatec 15%
NDC: 66104-6481 | Form: POWDER
Manufacturer: Phibro Animal Health
Category: animal | Type: OTC ANIMAL DRUG LABEL
Date: 20260213

ACTIVE INGREDIENTS: LASALOCID SODIUM 90.7 g/0.45 kg

Avatec 15% (Lasalocid Sodium)

ABUSE

(For Animal Use Only)
Lasalocid (as lasalocid sodium) ..... 15%
in a roughage product carrier

Marketed by:
Phibro Animal Health Corporation
Teaneck, NJ 07666, USA

Phibro, Phibro logo and Avatec are trademarks owned by or licensed to
Phibro Animal Health Corporation or its affiliates.

Net 20 Kg

DESCRIPTION

Avatec 15 (Lasalocid Sodium)

INDICATIONS AND USAGE

For use in the manufacture of medicated feeds only.

For the prevention of coccidiosis in -

Broiler and fryer chickens: Eimeria tenella, E. necatrix, E. acervulina, E. brunetti, E. mivati, and E. maxima

Growing Turkeys: E. meleagrimitis, E. gallopavonis, E. adenoeides

Rabbits: E. stiedae

Chukar Partridges: E. legionensis

Avatec 15 Label